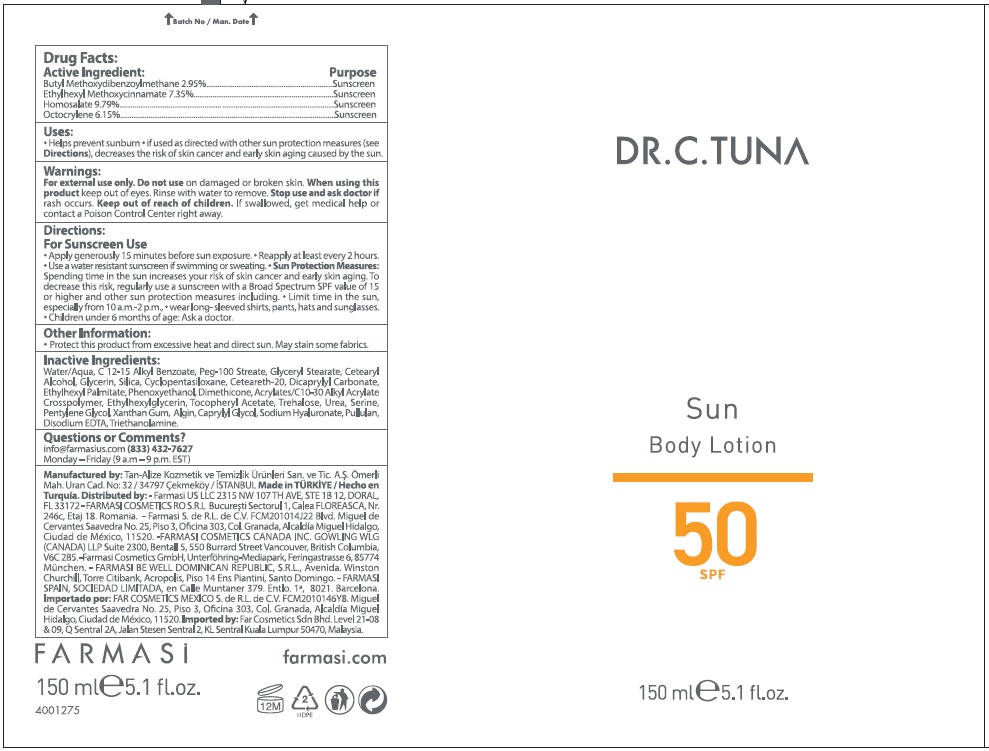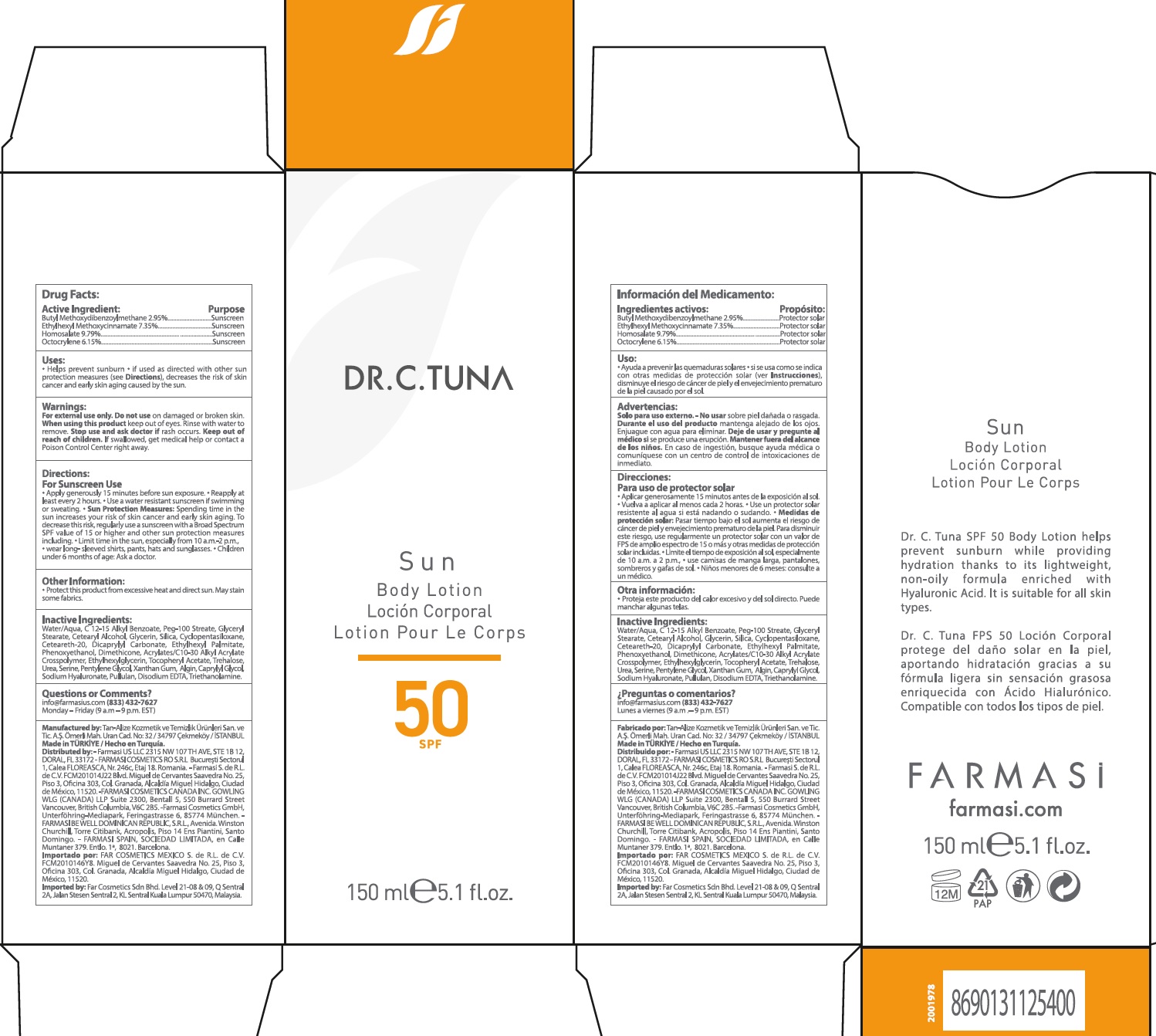 DRUG LABEL: Dr.C.Tuna Sun Body SPF50
NDC: 78317-036 | Form: CREAM
Manufacturer: Tan Alize Kozmetik ve Temizlik Urunleri Sanayi ve Ticaret Anonim Sirketi
Category: otc | Type: HUMAN OTC DRUG LABEL
Date: 20231105

ACTIVE INGREDIENTS: AVOBENZONE 29.5 mg/1 mL; OCTINOXATE 73.5 mg/1 mL; HOMOSALATE 97.9 mg/1 mL; OCTOCRYLENE 61.5 mg/1 mL
INACTIVE INGREDIENTS: WATER; ALKYL (C12-15) BENZOATE; PEG-100 STEARATE; GLYCERYL MONOSTEARATE; CETOSTEARYL ALCOHOL; GLYCERIN; SILICON DIOXIDE; CYCLOMETHICONE 5; POLYOXYL 20 CETOSTEARYL ETHER; DICAPRYLYL CARBONATE; ETHYLHEXYL PALMITATE; PHENOXYETHANOL; DIMETHICONE; ETHYLHEXYLGLYCERIN; .ALPHA.-TOCOPHEROL ACETATE; TREHALOSE; UREA; SERINE; PENTYLENE GLYCOL; XANTHAN GUM; SODIUM ALGINATE; CAPRYLYL GLYCOL; HYALURONATE SODIUM; PULLULAN; EDETATE DISODIUM ANHYDROUS; TROLAMINE

Dr.C.Tuna Sun Body Lotion SPF50

Active Ingredient:

Butyl Methoxydibenzoylmethane 2.95%

Ethylhexyl Methoxycinnamate 7.35%

Homosalate 9.79%

Octocrylene 6.15%

Purpose

Sunscreen

Uses

- Helps prevent sunburn
- if used as directed with other sun protection measures (see), decreases the risk of skin cancer and early skin aging caused by the sun. Directions

Warnings

For external use only.

Do not use

on damaged or broken skin.

When using this product

keep out of eyes. Rinse with water to remove.

Stop use and ask doctor if

rash occurs.

Keep out of reach of children.

If swallowed, get medical help or contact a Poison Control Center right away.

Directions

- For Sunscreen Use
- Apply generously 15 minutes before sun exposure.
- Reapply at least every 2 hours
- Use a water resistant sunscreen if swimming or sweating.
- Spending time in the sun increases your risk of skin cancer and early skin aging. To decrease this risk, regularly use a sunscreen with a Broad Spectrum SPF value of 15 or higher and other sun protection measures including Sun Protection Measures:
- Limit time in the sun, especially from 10 a.m. -2 p.m.,
- wear long-sleeved shirts, pants, hats and sunglasses.
- Children under 6 months of age: Ask a doctor.

Other Information:

- Protect this product from excessive heat and direct sun. May stain some fabrics.

Inactive Ingredients:

Water/Aqua, C12-15 Alkyl Benzoate, Peg-100 Stearate, Glyceryl Stearate, Cetearyl Alcohol, Glycerin, Silica, Cyclopentasiloxane, Ceteareth-20, Dicaprylyl Carbonate, Ethylhexyl Palmitate, Phenoxyethanol, Dimethicone, Acrylates/C10-30 Alkyl Acrylate Crosspolymer, Ethylhexylglycerin, Tocopheryl Acetate, Trehalose, Urea, Serine, Pentylene Glycol, Xanthan Gum, Algin, Caprylyl Glycol, Sodium Hyaluronate, Pullulan, Disodium EDTA, Triethanolamine.

Questions or Comments?

info@farmasius.com Monday - Friday (9 a.m. - 9 p.m. EST) (833) 432-7627